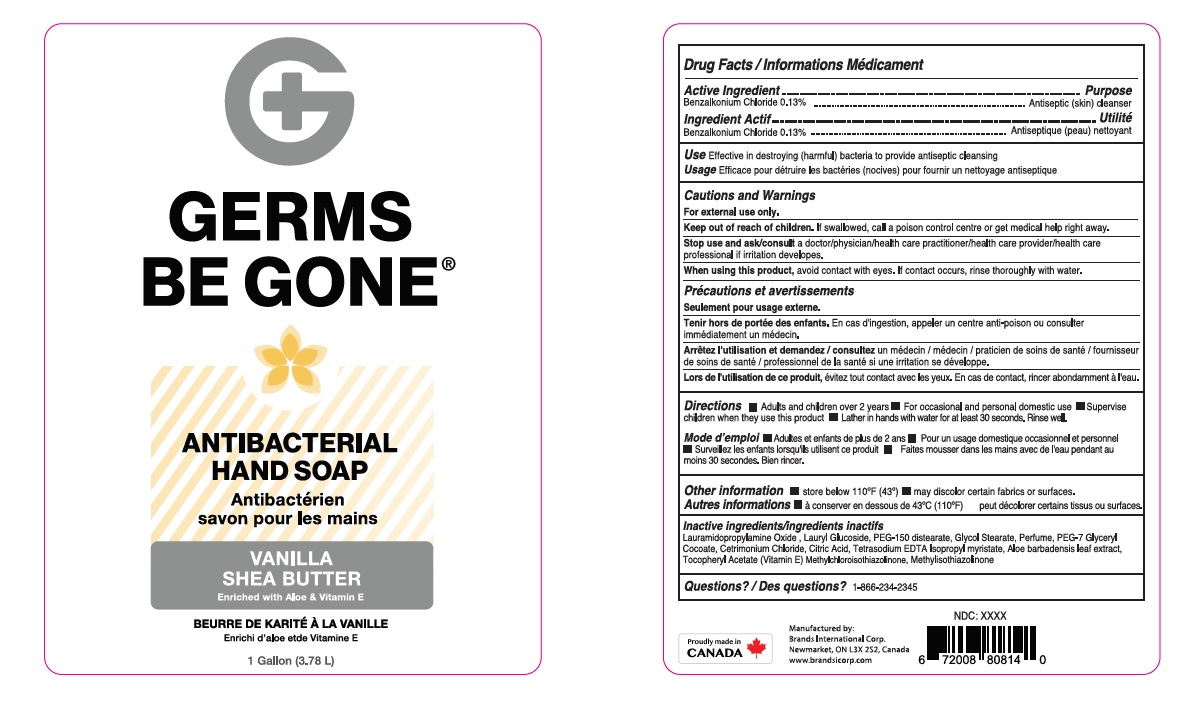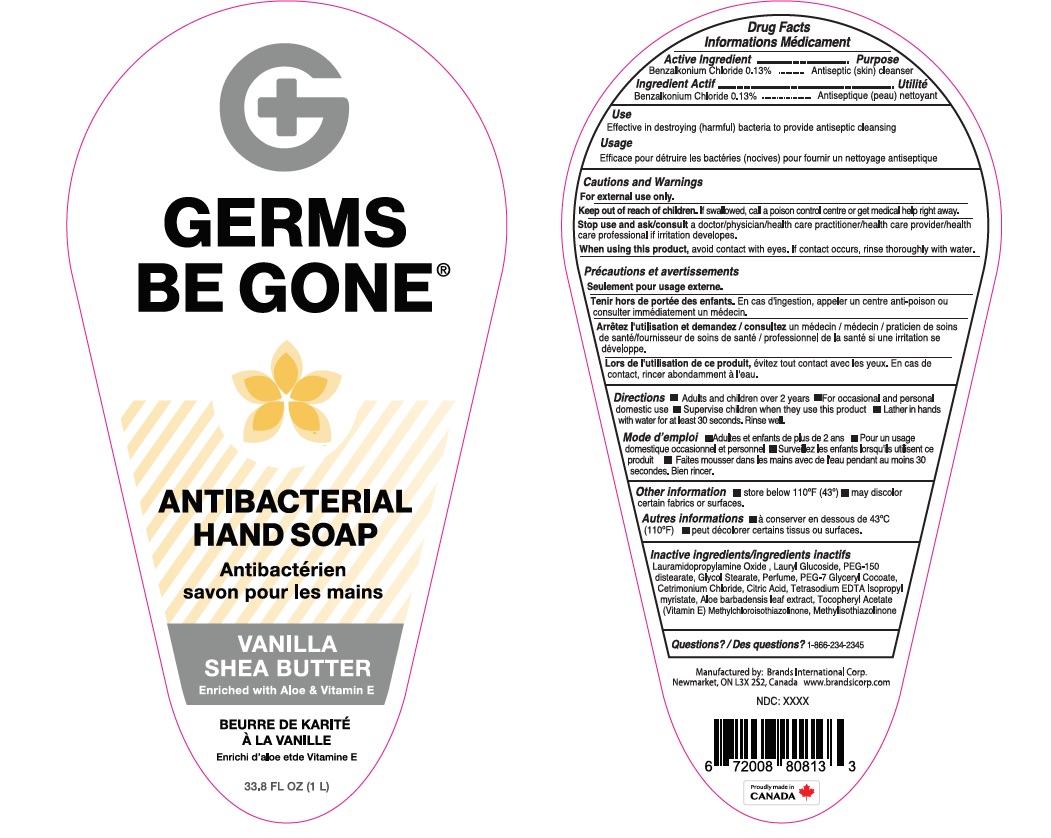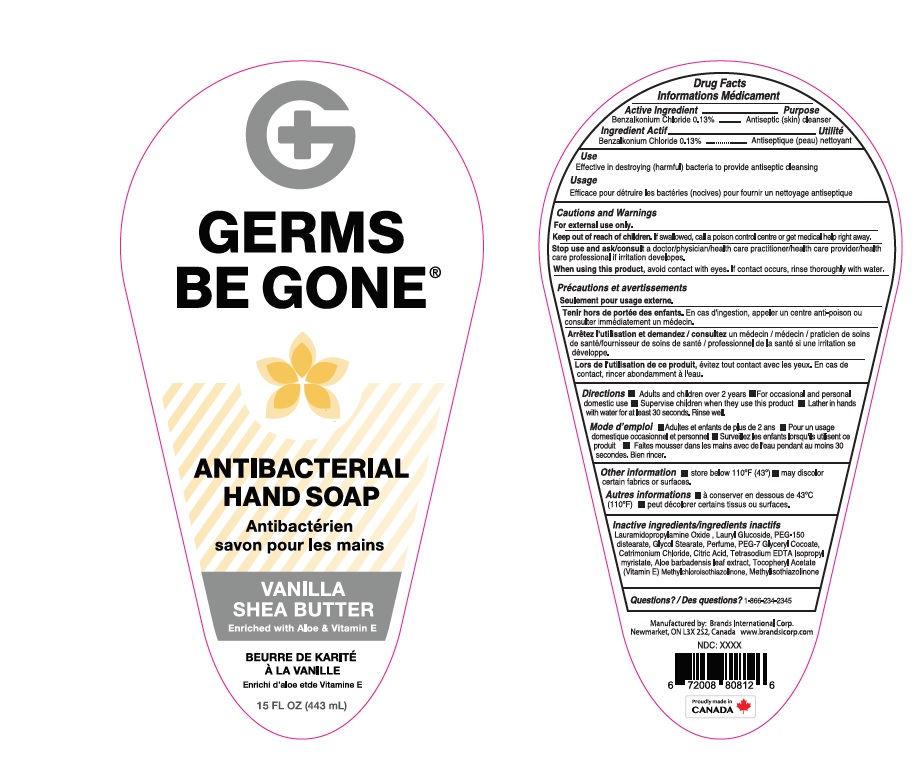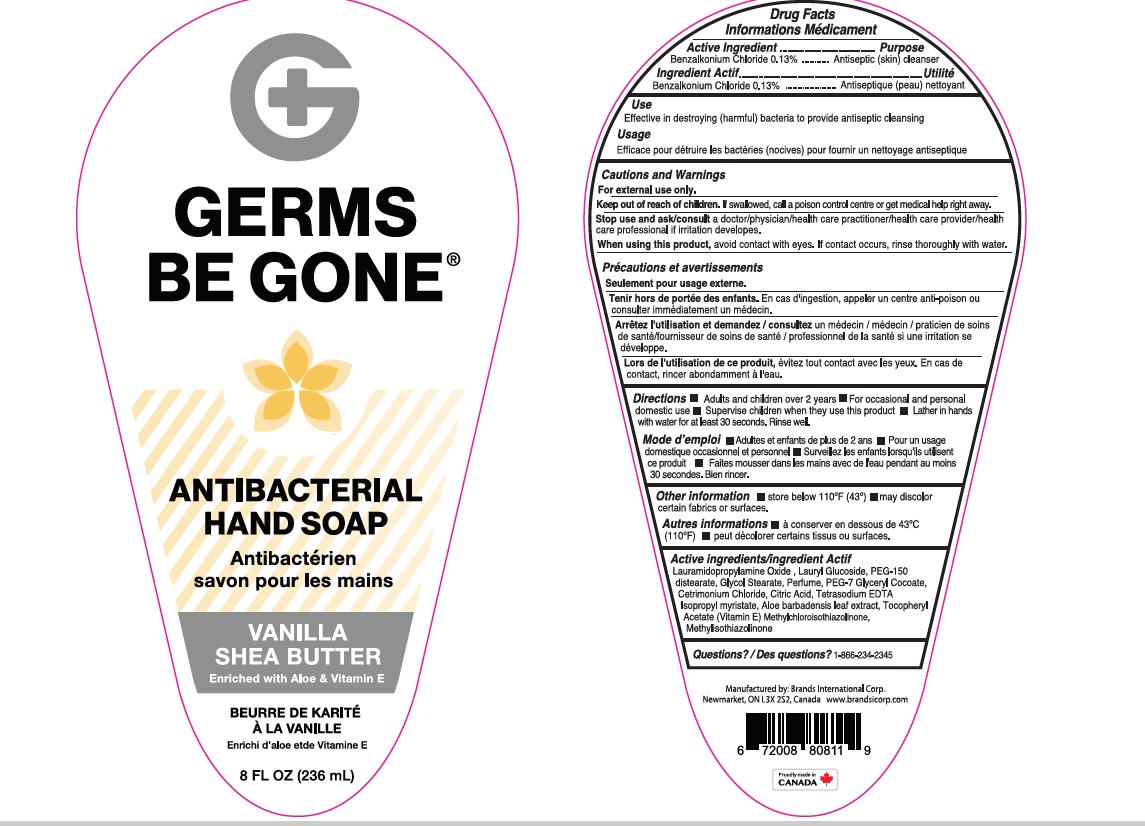 DRUG LABEL: Antibacterial
NDC: 50157-508 | Form: LIQUID
Manufacturer: Brands International Corporation
Category: otc | Type: HUMAN OTC DRUG LABEL
Date: 20200914

ACTIVE INGREDIENTS: BENZALKONIUM CHLORIDE 1.3 mg/1 mL
INACTIVE INGREDIENTS: CETRIMONIUM CHLORIDE; ISOPROPYL MYRISTATE; GLYCOL STEARATE; LAURAMIDOPROPYLAMINE OXIDE; PEG-7 GLYCERYL COCOATE; DITETRACYCLINE TETRASODIUM EDETATE; METHYLCHLOROISOTHIAZOLINONE; METHYLISOTHIAZOLINONE; .ALPHA.-TOCOPHEROL ACETATE; ALOE VERA LEAF; ANHYDROUS CITRIC ACID; PEG-150 DISTEARATE; LAURYL GLUCOSIDE

Germs be Gone Antibacterial Hand Soap: Vanilla and Shea Butter

ACTIVE INGREDIENT

Benzalkonium Chloride - 0.13%

Purpose - Antiseptic Skin cleanser

INDICATIONS AND USAGE

Uses for handwashing or decrease bacteria to the skin

Warnings For external use only

Stop use and ask a doctor if irritation or redness develops

When using this product

- do not get it into eyes. If contact occurs, rinse eye thoroughly with water

Keep out of reach of children If swallowed get medical help or contact a Poison Control Center right away

Directions

- wet hands
- apply palmful to hands
- scrub thoroughly
- rinse
- For occasional and personal domestic use
- Supervise children when they use this product.

INACTIVE INGREDIENT

Lauramidopropylamine oxide, lauryl glucoside, PEG-150 distearate, glycol stearate, perfume, PEG-7 glycerly cocoate, centrimonium chloride, Citric Acid, Glycerin, Tetrasodium EDTA, Methylchloroisothiazolinone, Methylisothiazolinone,